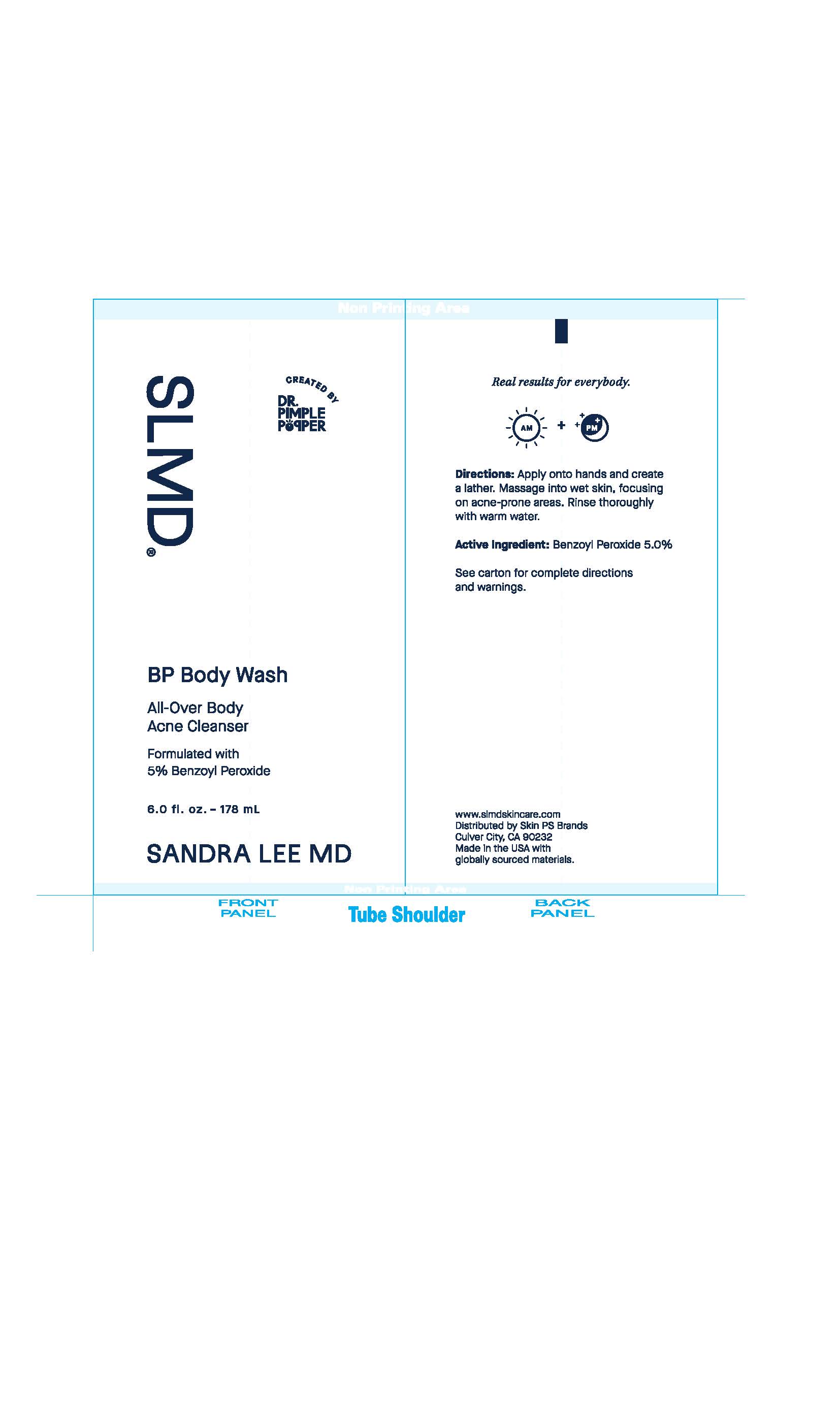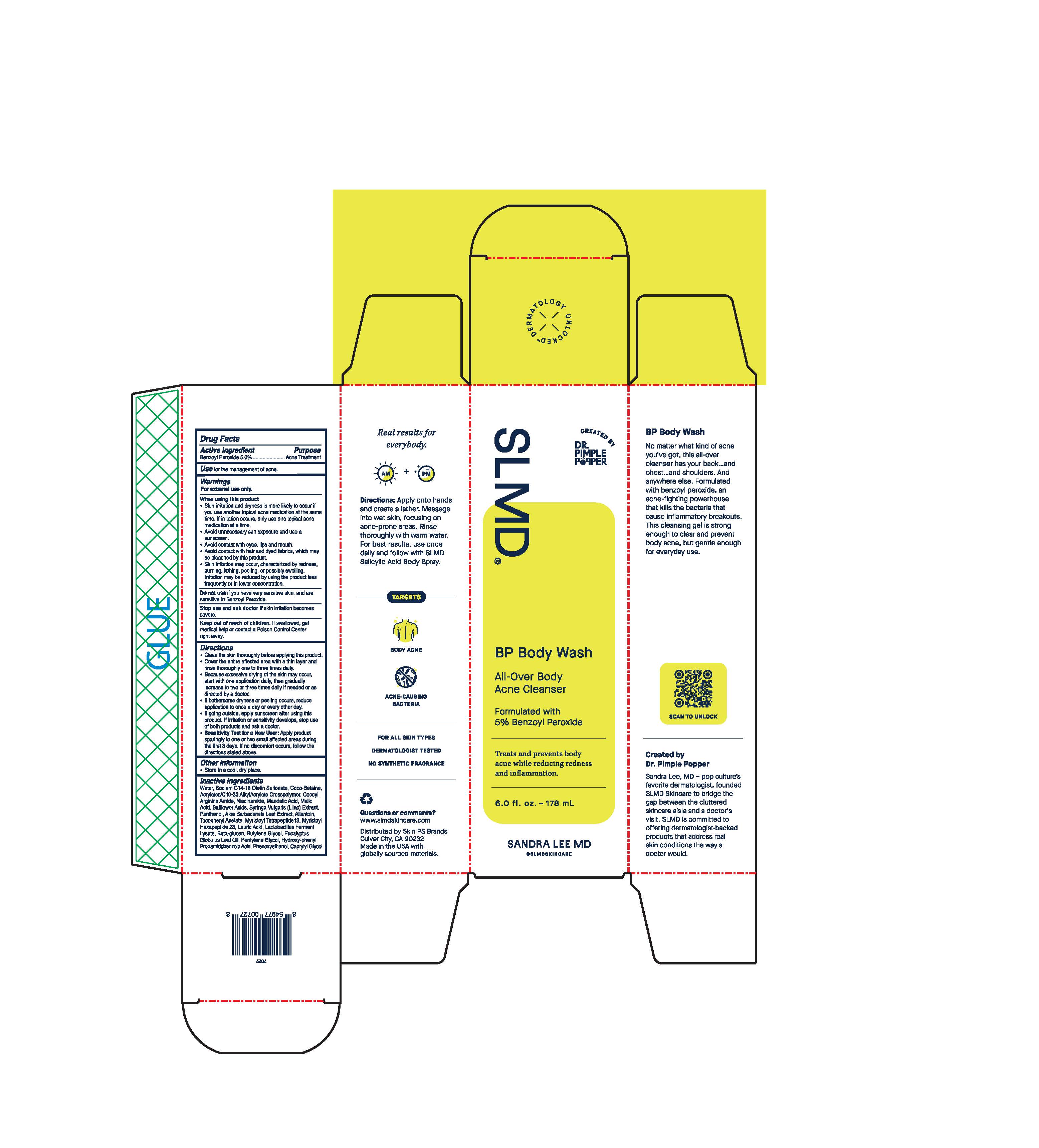 DRUG LABEL: BP Body Wash
NDC: 73318-7005 | Form: GEL
Manufacturer: Skin PS Brands
Category: otc | Type: HUMAN OTC DRUG LABEL
Date: 20251230

ACTIVE INGREDIENTS: BENZOYL PEROXIDE 50 mg/1 g
INACTIVE INGREDIENTS: ACRYLATES/C10-30 ALKYL ACRYLATE CROSSPOLYMER (60000 MPA.S); ARGININE; NIACINAMIDE; MANDELIC ACID; MALIC ACID; SAFFLOWER ACID; SYRINGA VULGARIS WHOLE; ALOE VERA LEAF; WATER; ALLANTOIN; HYDROXYPHENYL PROPAMIDOBENZOIC ACID; EUCALYPTUS OIL; PANTHENOL; SODIUM CARBOXYMETHYL .BETA.-GLUCAN (DS 0.65-0.85); PHENOXYETHANOL; .ALPHA.-TOCOPHEROL ACETATE; LIMOSILACTOBACILLUS FERMENTUM; LAURIC ACID; MYRISTOYL HEXAPEPTIDE-12, (VAL-GLY-VAL-ALA-PRO-GLY)-; MYRISTOYL TETRAPEPTIDE-4; COCO-BETAINE; SODIUM C14-16 OLEFIN SULFONATE

BP Body Wash

Active Ingredient

Benzoyl Peroxide 5.0%

Purpose

Acne Treatment

Use

for the management of acne.

Warnings

For external use only.

When using this product

- Skin irritation and dryness is more likely to occur if you use another topical acne medication at the same time. If irritation occurs, only use one topical acne medication at a time.
- avoid unnecessary sun exposure and use a sunscreen.
- avoid contact with eyes, lips and mouth.
- avoid contact with hair and dyed fabrics, which may be bleached by this product.
- Skin irritation may occur, characterized by redness, burning, itching, peeling, or possibly swelling. Irritation may be reduced by using the product less frequently or in a lower concentration.

Do not use

if you have very sensitive skin, and are sensitive to Benzyl Peroxide.

Stop use and ask a doctor if

skin irritation becomes severe.

Keep out of reach of children.

If swallowed, get medical help or contact a Poison Control Center right away.

Directions

- Clean the skin thoroughly before applying this product.
- Cover the entire affected area with a thin layer and rinse thoroughly one to three times daily.
- Because excessive drying of the skin may occur, start with one application daily, then gradually increase to two or three daily if needed or as directed by a doctor.
- If bothersome dryness or peeling occurs, reduce application to once a day or every other day.
- If going outside, apply sunscreen after using this product. If irritation or sensitivity develops, stop use of both products and ask a doctor.
- Sensitivity Test for a New User: Apply product sparingly to one or two small affected areas during the first three days. if no discomfort occurs, follow the directions stated above.

Other Information

- Store in a cool, dry place.

Inactive Ingredients

Water, Sodium C14-15 Olefin Sulfonate, Coco-Betaine, Acrylates/C10-30 Alkyl Acrylate Crosspolymer, Cocoyl Arginine Amide, Niacinamide, Mandelic Acid, Malic Acid, Safflower Acids, Syringa Vulgaris (Lilac) Extract, Panthenol, Aloe Barbadensis Leaf Extract, Allantoin, Tocopheryl Acetate, Myristoyl Tetrapeptide 13, Myristoyl Hexapeptide 23, Lauric Acid, Lactobacillus Ferment Lysate, Beta-glucan, Butylene Glycol, Eucalyptus Globulus Leaf Oil, Pentylene Glycol, Hydroxy-phenyl Propamidobenzoic Acid, Phenoxyethanol, Caprylyl Glycol.

Questions or comments?

www.slmdskincare.com

Distributed by Skin PS Brands

Culver City, CA 90232

Made in the USA with globally sourced materials.

SLMD Sandra Lee MD

Created by Dr. Pimple Popper

BP Body Wash

All-Over Body

Acne Cleanser

Formulated with

5% Benzoyl Peroxide

Treats and prevents body acne while reducing redness and inflammation.

6.0 fl. oz. - 178 mL

SANDRA LEE MD

@SLMDSKINCARE

Unit Carton:

Primary:

Real results for everybody.

AM + PM

Directions: Apply onto hands and create a lather. Massage into wet skin, focusing on acne-prine areas. Rinse thoroughly with warm water. For best results, use once daily and follow with SLMD Salicylic Acid Body Spray.

TARGETS

BODY ACNE

ACNE-CAUSING BACTERIA

FOR ALL SKIN TYPES

DERMATOLOGIST TESTED

NO SYNTHETIC FRAGRANCE

Questions or comments?

www.slmdskincare.com

Distributed by Skin PS Brands

Culver City, CA 90232

Made in the USA with globally sourced materials.

BP Body Wash

No matter what kind of acne you've got, this all-over cleanser has your back..and chest..and shoulders. And anywhere else. Formulated with benzoyl peroxide, an acne-fighting powerhouse that kills the bacteria that cause inflammatory breakouts. This cleansing gel is strong enough to clear and prevent body acne, but gentle enough for everyday use.

Created by Dr. Pimple Popper

Sandra Lee, MD - pop culture's favorite dermatologist, founded SLMD Skincare to bridge the gap between the cluttered skincare aisle and a doctor's visit. SLMD is committed to offering dermatologist-backed products that address real skin conditions the way a doctor would.